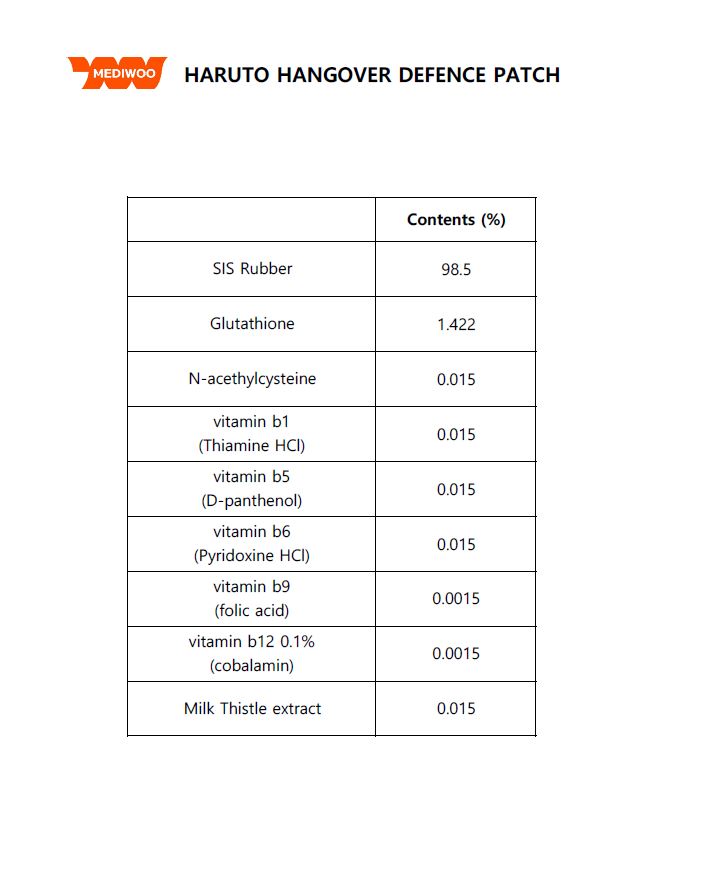 DRUG LABEL: HARUTO HANGOVER DEFENCEPATCH
NDC: 80094-0001 | Form: PATCH
Manufacturer: YOUNGWOO CO.,LTD
Category: otc | Type: HUMAN OTC DRUG LABEL
Date: 20220112

ACTIVE INGREDIENTS: GLUTATHIONE 1.422 mg/100 mg
INACTIVE INGREDIENTS: THIAMINE HYDROCHLORIDE

ACTIVE INGREDIENT

glutathione

INACTIVE INGREDIENT

N-acethylcysteine
vitamin b1 (Thiamine HCl)
vitamin b5 (D-panthenol)
vitamin b6 (Pyridoxine HCl)
vitamin b9 (folic acid)
vitamin b12 0.1% (cobalamin)
Milk Thistle extract

PURPOSE

Hangover relief

Keep out of reach of the children

INDICATIONS AND USAGE

Stick the patch to target areas of concern and gently press down on the patch

WARNINGS

1. Do not use in the following cases(Eczema and scalp wounds)
2.Side Effects
1)Due to the use of this druf if rash, irritation, itching and symptopms of hypersnesitivity occur dicontinue use and consult your phamacisr or doctor
3.General Precautions
1)If in contact with the eyes, wash out thoroughty with water If the symptoms are servere, seek medical advice immediately
2)This product is for exeternal use only. Do not use for internal use
4.Storage and handling precautions
1)If possible, avoid direct sunlight and store in cool and area of low humidity
2)In order to maintain the quality of the product and avoid misuse
3)Avoid placing the product near fire and store out in reach of children

DOSAGE AND ADMINISTRATION

for external use only